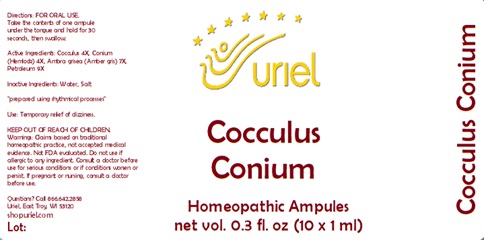 DRUG LABEL: Cocculus Conium
NDC: 48951-3263 | Form: LIQUID
Manufacturer: Uriel Pharmacy Inc.
Category: homeopathic | Type: HUMAN OTC DRUG LABEL
Date: 20240130

ACTIVE INGREDIENTS: ANAMIRTA COCCULUS WHOLE 4 [hp_X]/1 mL; CONIUM MACULATUM ROOT 4 [hp_X]/1 mL; AMBERGRIS 7 [hp_X]/1 mL; LIQUID PETROLEUM 9 [hp_X]/1 mL
INACTIVE INGREDIENTS: WATER; SODIUM CHLORIDE

Cocculus Conium

INDICATIONS AND USAGE

Directions: FOR ORAL USE.

DOSAGE AND ADMINISTRATION

Take the contents of one ampule under the tongue and hold for 30 seconds, then swallow.

ACTIVE INGREDIENT

Active Ingredients: Cocculus e fruct. 4X, Conium mac. 4X, Ambra grisea 7X, Petroleum 9X

Inactive Ingredients: Water, Salt

"prepared using rhythmical processes'

PURPOSE

Use: Temporary relief of dizziness.

KEEP OUT OF REACH OF CHILDREN.

WARNINGS

Warnings: Claims based on traditional homeopathic practice, not accepted medical evidence. Not FDA evaluated. Do not use if allergic to any ingredient. Consult a doctor before use for serious conditions or if conditions worsen or persist. If pregnant or nursing, consult a doctor before use.

QUESTIONS

Questions? Call 866.642.2858 Uriel, East Troy, WI 53120 shopuriel.com